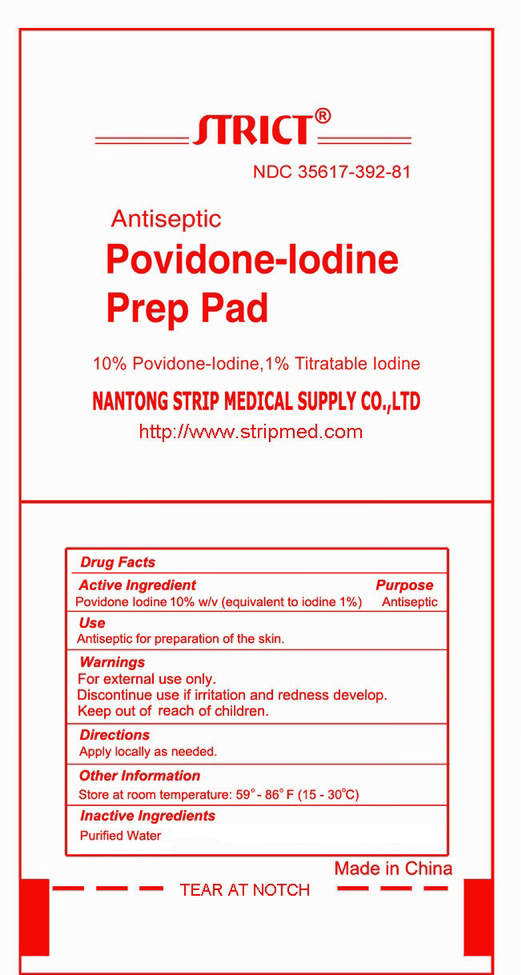 DRUG LABEL: Povidone-Iodine Prep Pad
NDC: 35617-392 | Form: SWAB
Manufacturer: NANTONG STRIP MEDICAL SUPPLY CO.,LTD. 
Category: otc | Type: HUMAN OTC DRUG LABEL
Date: 20120131

ACTIVE INGREDIENTS: POVIDONE-IODINE 10 mL/1 1
INACTIVE INGREDIENTS: WATER 89.96 mL/1 1; Citric acid 0.01 mL/1 1; SODIUM PHOSPHATE, DIBASIC, DIHYDRATE 0.01 mL/1 1; NONOXYNOL-9 0.01 mL/1 1; Sodium Hydroxide 0.01 mL/1 1

Drug Fact

Active Ingredient

POVIDONE-IODINE 10% W/v (equivalent to iodine 1%)

Purpose

Antiseptic

Warnings

For External use only.
Discontinue use if irritation and redness develop

Keep out of reach of children

If swallowed,get medical help or contact a Poison Control Center right away.

Directions

Apple locally as needed.

Other information

Store at room temperature:59o-86oF(15--30℃)

Use

Antiseptic for preparation of the skin

Inactive Ingredients

Water，Citric acid, Disodium phosphate, Nonoxynol-9, Sodium Hydroxide,Purified Water

PACKAGE LABEL

Enter section text here